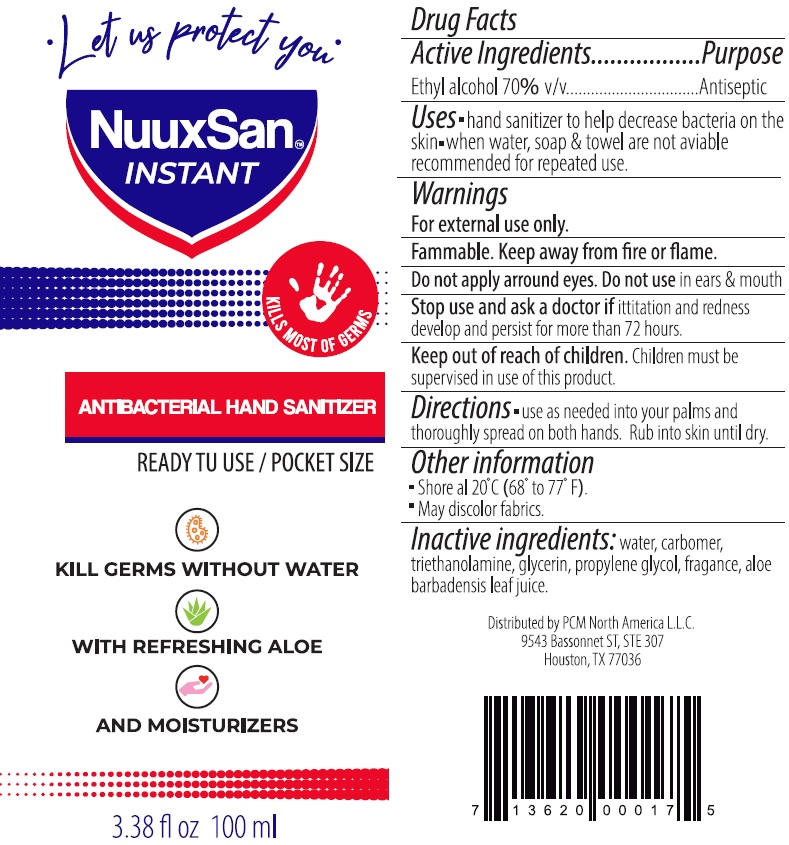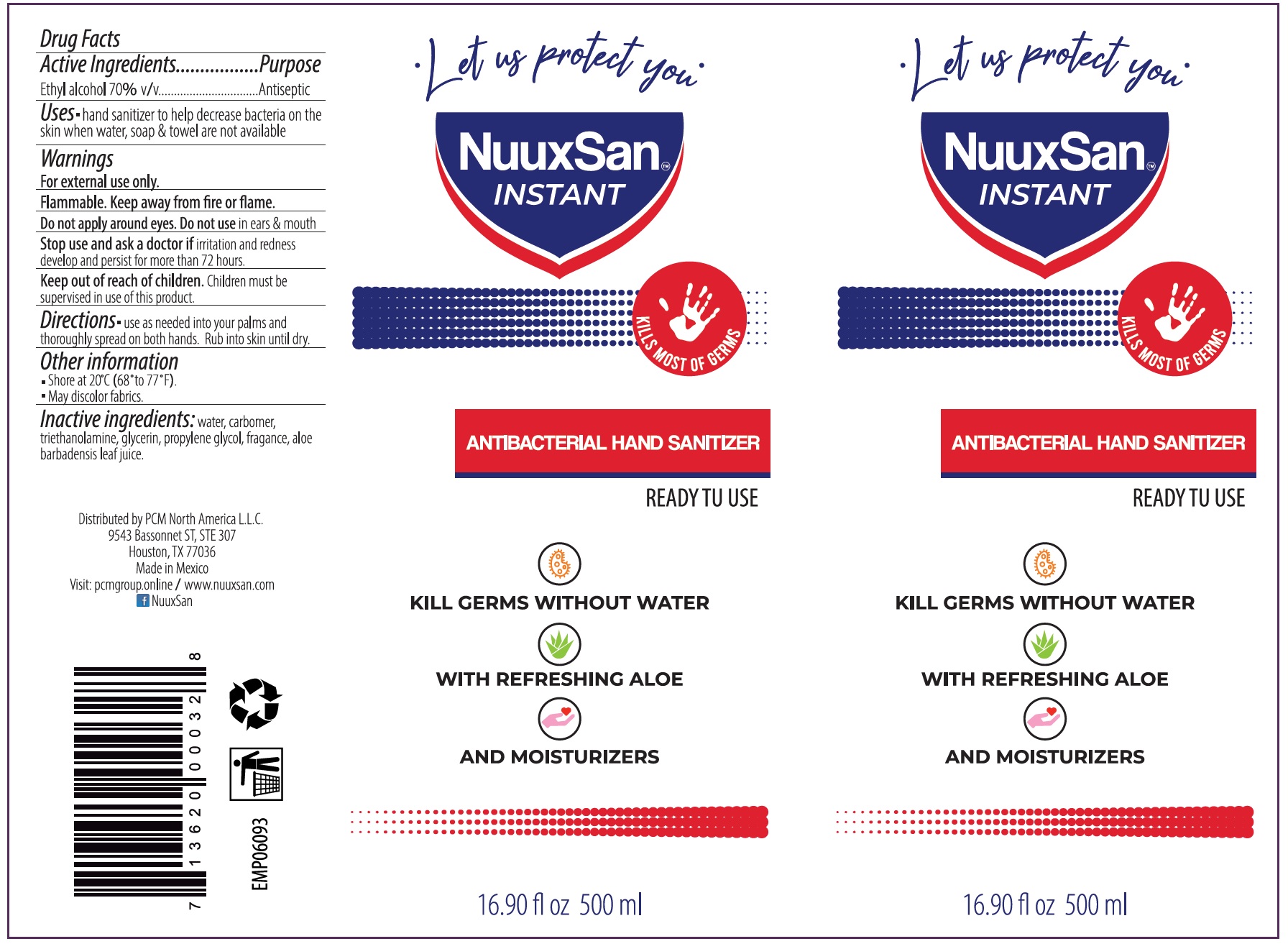 DRUG LABEL: NuuxSan Instant Hand Sanitizer
NDC: 72758-003 | Form: LIQUID
Manufacturer: Albek de Mexico, S.A. de C.V.
Category: otc | Type: HUMAN OTC DRUG LABEL
Date: 20200608

ACTIVE INGREDIENTS: ALCOHOL 0.7 mL/1 mL
INACTIVE INGREDIENTS: WATER; CARBOMER HOMOPOLYMER, UNSPECIFIED TYPE; TROLAMINE; GLYCERIN; PROPYLENE GLYCOL; ALOE VERA LEAF

NuuxSan Instant Hand Sanitizer

Active Ingredients

Ethyl alcohol 70% v/v

Purpose

Antiseptic

Uses

- hand sanitizer to help decrease bacteria on the skin
- when water, soap & towel are not aviable recommended for repeated use.

Warnings

For external use only.

Flammable. Keep away from fire or flame.

Do not apply arround eyes.

Do not use

in ears & mouth

Stop use and ask a doctor if

ittitation and redness develop and persist for more than 72 hours.

Keep out of reach of children.

Children must be supervised in use of this product.

Directions

- use as needed into your palms and thoroughly spread on both hands. Rub into skin until dry.

Other information

- Shore al 20°C (68° to 77°F).
- May discolor fabrics.

Inactive ingredients:

water, carbomer, triethnolamine, glycerin, propylene glycol, fragrance, aloe barbadensis leaf juice.